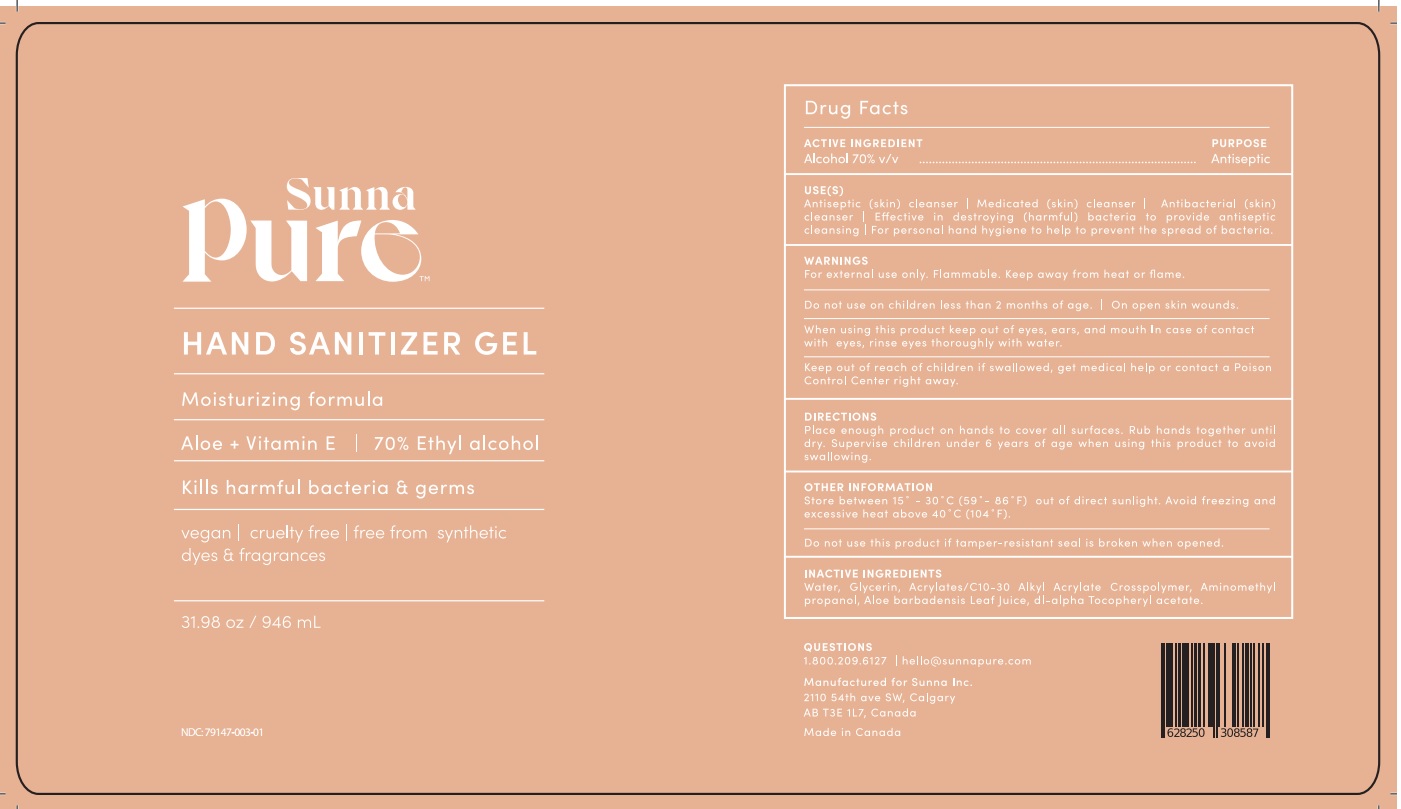 DRUG LABEL: Sunna Pure Hand Sanitizer Gel
NDC: 79147-003 | Form: GEL
Manufacturer: Spa Dent Inc.
Category: otc | Type: HUMAN OTC DRUG LABEL
Date: 20210104

ACTIVE INGREDIENTS: ALCOHOL 0.7 mL/1 mL
INACTIVE INGREDIENTS: WATER; ALOE VERA LEAF; .ALPHA.-TOCOPHEROL; GLYCERIN; AMINOMETHYLPROPANOL

Sunna Pure Hand Sanitizer Gel

ACTIVE INGREDIENT

Alcohol 70% v/v

PURPOSE

Antiseptic

USE(S)

• Antiseptic (skin) cleanser • Medicated (skin) cleanser • Antibacterial (skin) cleanser • Effective in destroying (harmful) bacteria to provide antiseptic cleansing • For personal hand hygiene to help prevent the spread of bacteria

WARNINGS

• For external use only. Flammable. Keep away from heat or flame.

Do not use

• in children less than 2 months of age • on open skin wounds.

When using this product

• keep out of eyes, ears, and mouth • In case of contact with eyes, rinse eyes thoroughly with water.

Stop use and ask a doctor

if irritation or rash occurs. These may be signs of a serious condition.

Keep out of reach of children.

If swallowed, get medical help or contact a Poison Control Center right away.

DIRECTIONS

• Place enough product on hands to cover all surfaces. Rub hands together until dry. • Supervise children under 6 years of age when using this product to avoid swallowing.

OTHER INFORMATION

• Store between 15° - 30° C (59° - 86° F) out of direct sunlight • Avoid freezing and excessive heat above 40° C (104° F).

Do not use this product if tamper-resistant seal is broken when opened.

INACTIVE INGREDIENTS

Purified Water, Aloe Barbadensis Leaf Juice, Vitamin E, Glycerin, Carbomer Copolymer, Aminomethyl Propanol